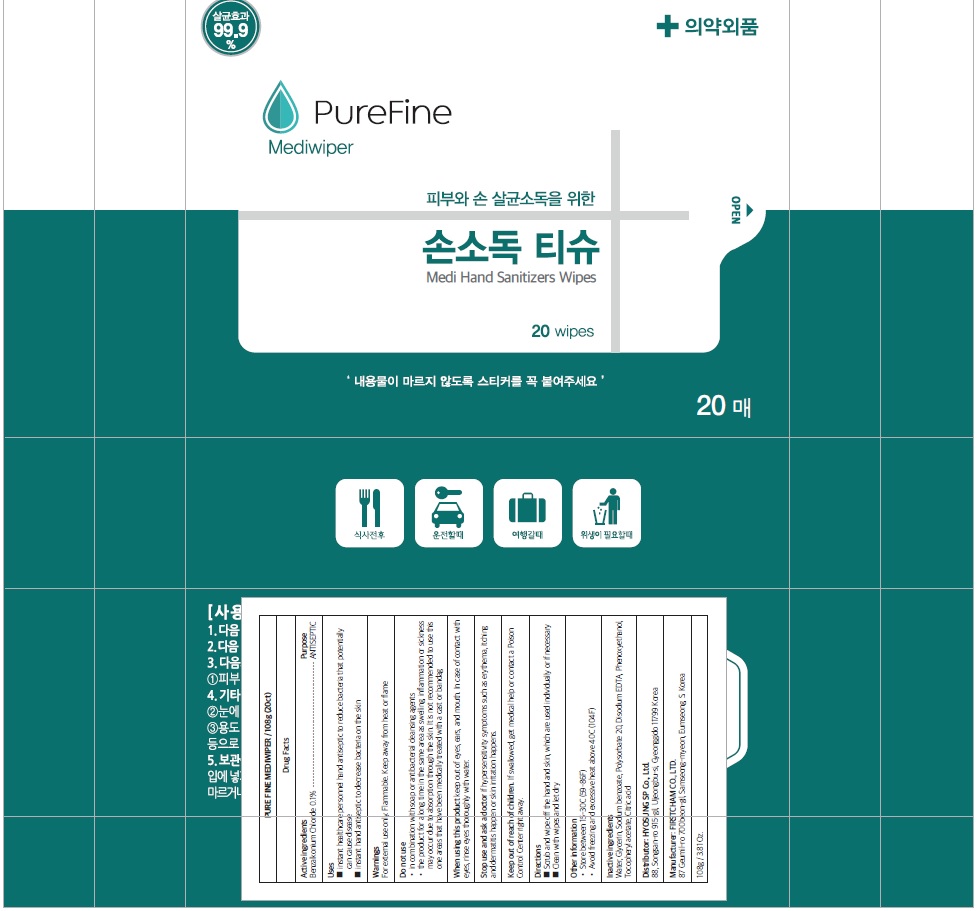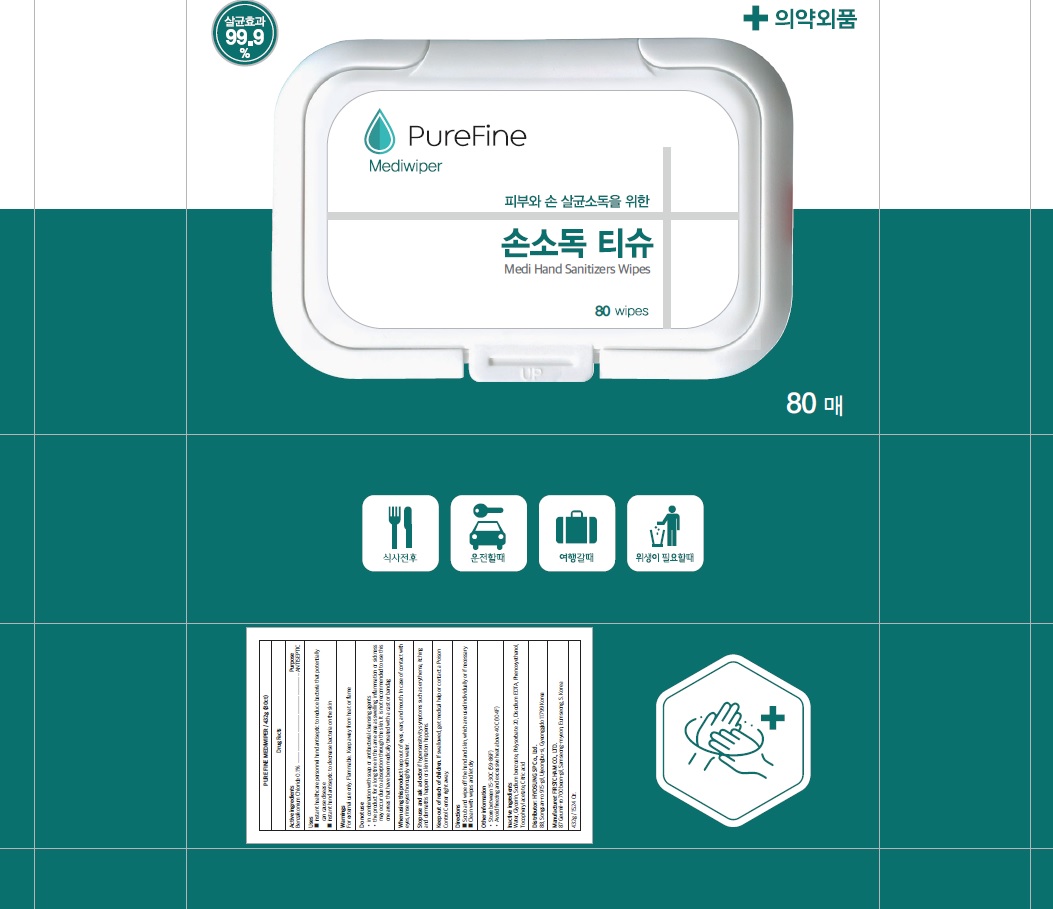 DRUG LABEL: PURE FINE MEDIWIPER
NDC: 76522-010 | Form: LIQUID
Manufacturer: Hyosung SP Co.,Ltd
Category: otc | Type: HUMAN OTC DRUG LABEL
Date: 20200424

ACTIVE INGREDIENTS: BENZALKONIUM CHLORIDE 0.1 g/100 g
INACTIVE INGREDIENTS: WATER; Glycerin; SODIUM BENZOATE; Polysorbate 20; EDETATE DISODIUM ANHYDROUS; Phenoxyethanol; .ALPHA.-TOCOPHEROL ACETATE; CITRIC ACID MONOHYDRATE

Drug Facts

ACTIVE INGREDIENT

Active Ingredients: Benzalkonium Chloride 0.1%

INACTIVE INGREDIENT

Inactive Ingredients:

Water, Glycerin, Sodium benzoate, Polysorbate 20, Disodium EDTA, Phenoxyethanol, Tocopheryl acetate, Citric acid

PURPOSE

Purpose: antiseptic

Keep out of reach of children. If swallowed, get medical help or contact a Poison Control Center right away.

Uses

■ instant healthcare personnel hand antiseptic to reduce bacteria that potentially can cause disease
■ instant hand antiseptic to decrease bacteria on the skin

WARNINGS

For external use only. Flammable. Keep away from heat or flame
--------------------------------------------------------------------------------------------------------
Do not use
• in combination with soap or antibacterial cleansing agents
• the product for a long time in the same area as swelling, inflammation or sickness may occur due to absorption through the skin. It is not recommended to use this one areas that have been medically treated with a cast or bandage
--------------------------------------------------------------------------------------------------------
When using this product keep out of eyes, ears, and mouth. In case of contact with eyes, rinse eyes thoroughly with water.
--------------------------------------------------------------------------------------------------------
Stop use and ask a doctor if hypersensitivity symptoms such as erythema, itching and dermatitis happen or skin irritation happens.

Directions

■ Scrub and wipe off the hand and skin, which are used individually or if necessary
■ Clean with wipes and let dry

Other information

• Store between 15-30C (59-86F)
• Avoid freezing and excessive heat above 40C (104F)